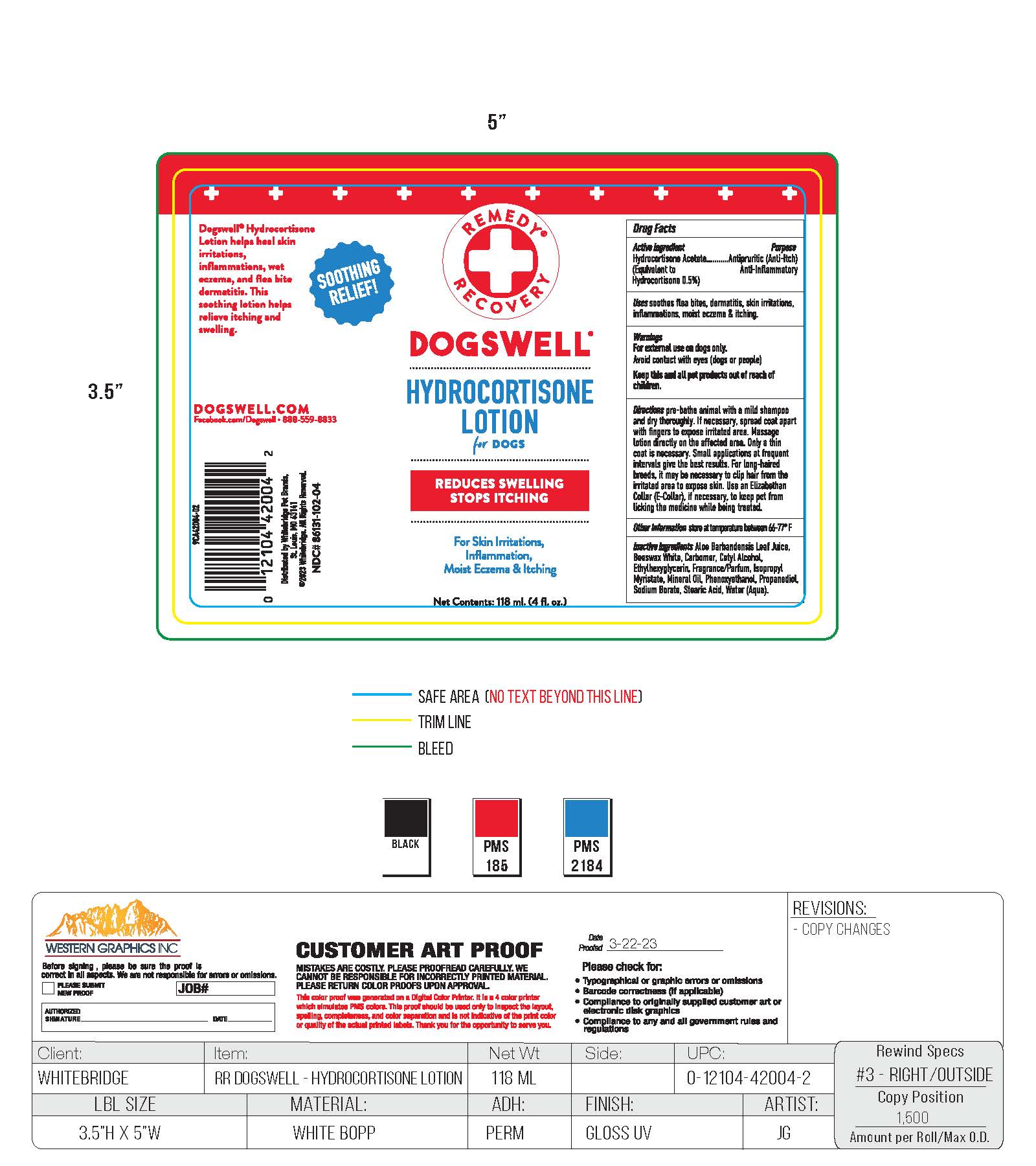 DRUG LABEL: Hydrocortisone
NDC: 86131-102 | Form: LOTION
Manufacturer: Whitebridge Pet Brands
Category: animal | Type: OTC ANIMAL DRUG LABEL
Date: 20260123

ACTIVE INGREDIENTS: HYDROCORTISONE ACETATE 0.5 mg/100 mL
INACTIVE INGREDIENTS: WATER; CARBOMER 934; ISOPROPYL MYRISTATE; STEARIC ACID; WHITE WAX; CETYL ALCOHOL; MINERAL OIL; ALOE VERA LEAF; SODIUM BORATE; PROPANEDIOL; PHENOXYETHANOL; ETHYLHEXYLGLYCERIN

Hydrocortisone Lotion

DRUG FACTS

Active Ingredients

Hydrocortisone Acetate

(Equivalent to Hydrocortisone 0.5%)

Purpose

Antipruritic (Anti-Itch)

Anti-Inflammatory

Uses

soothes flea bites, dermatitis, skin irritations, inflammations, moist eczema & itching.

Warnings

For external use on dogs only.

Avoid contact with eyes (dogs or people)

Keep this and all pet products out of reach of childern.

Directions

pre-bathe animal with a mild shampoo and dry thoroughly. If necessary, spread coat apart with fingers to expose irritated area. Massage lotion directly on the affected area. Only a thin coat is necessary. Small applications at frequent intervals gives the best results. For long-haired breeds, it may be necessary to clip hair from the irritated area to expose skin. Use an Elizabethan Collar (E-Collar), if necessary, to keep pet from licking the medicine while being treated.

Other information

store at temperature between 66-77 F

Inactive ingredients

Aloe Barbandensis Leaf Juice, Beeswax White, Carbomer, Cetyl Alcohol, Ethylhexyglycerin, Fragrance/Parfum, Isopropyl Myristate, Mineral Oil, Phenoxyethanol, Propanediol, Sodium Borate, Stearic Acid, Water (Aqua).

SOOTHING RELIEF!

Dogswell Hydrocortisone Lotion helps heal skin irritations, inflammations, wet eczema, and flea bite dermatitis. This soothing lotion helps relieve itching and swelling.

DOGSWELL.COM

Facebook.com/Dogswell 888-55-8833

Distrubuted by Whitebridge Pet Brands,

St. Louis, MO 63141

2020 Whitebridge. All Right Reserved.

NDC# 86131-102-04

PACKAGE LABEL

REMEDY RECOVERY

DOGSWELL

HYDROCORTISONE LOTION

for DOGS

REDUCES SWELLING STOPS ITCHING

For Skin Irritations, Inflammation, Moist Eczema & Itching

Net Contents: 118 ml. (4 fl. oz.)